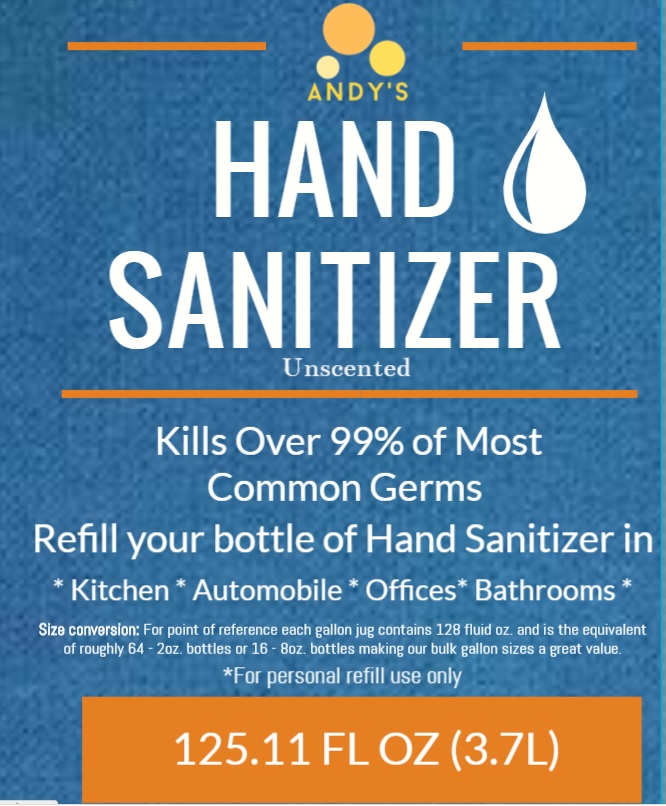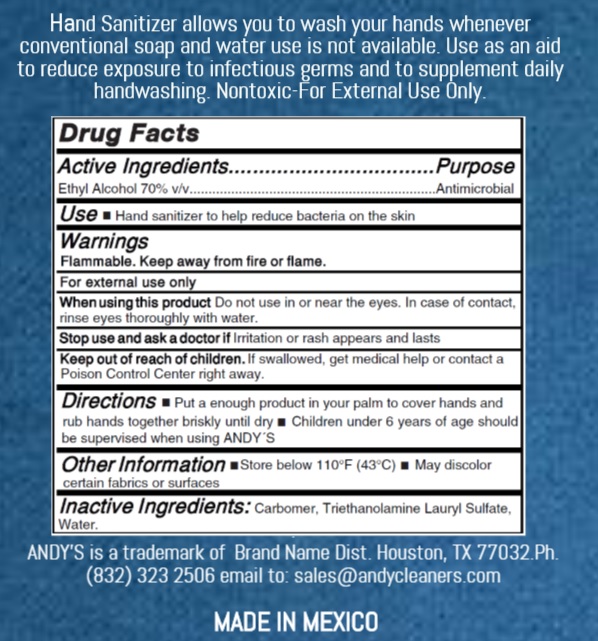 DRUG LABEL: Andys
NDC: 73755-110 | Form: GEL
Manufacturer: Brand Name Distributors
Category: otc | Type: HUMAN OTC DRUG LABEL
Date: 20200329

ACTIVE INGREDIENTS: ALCOHOL 0.7 mL/1 mL
INACTIVE INGREDIENTS: WATER O-18 1 mL/1 mL; TROLAMINE 1 mL/1 mL; CARBOMER 1342 1 mL/1 mL

Active Ingredient

Ethyl Alcohol 70% .........................Antimicrobial

DIRECTIONS AND USD

USE Hand Sanitizer to help reduce bacteria on the skin

INDICATION Put enough product in your palm to cover hands and rub hands together briskly until dry

INACTIVE INGREDIENTS

Carbomer, Triethanolamine Lauryl Sulfate, water

WARNING

Flammable. Keep away from fire or flame. For external use only. When using this product: Don't use in or near the eyes.

In the case of contact, rinse eyes thoroughly with water. Stop use and ask a doctor if irritation or rash appears and lasts.

Keep Out of Reach of Children. If swallowed, get medical help or contact poison control center right away

PURPOSE

Antimicrobial

DOSAGE

USE Hand Sanitizer to help reduce bacteria on the skin

INDICATION Put enough product in your palm to cover hands and rub hands together briskly until dry

ANDY's HAND SANITIZER Unscented

Kills Over 99% of Most Common Germs

Refill your bottle of Hand Sanitizer in

* Kitchen * Automobile * Offices* Bathrooms *

125.11 FL OZ (3.7L)